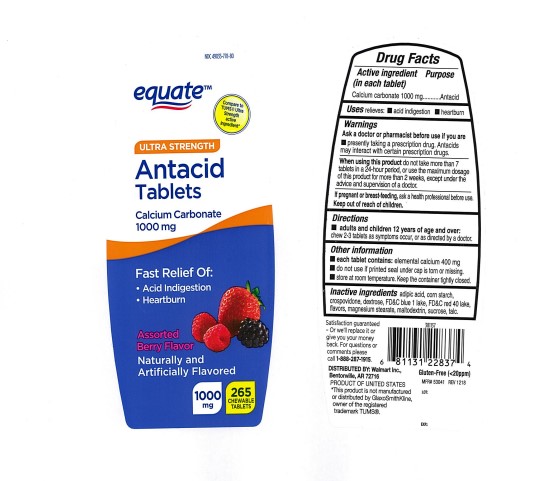 DRUG LABEL: Equate Ultra Stregth Antacid
NDC: 49035-778 | Form: TABLET, CHEWABLE
Manufacturer: Wal-Mart Stores, Inc.
Category: otc | Type: Human OTC Drug Label
Date: 20251203

ACTIVE INGREDIENTS: CALCIUM CARBONATE 1000 mg/1 1
INACTIVE INGREDIENTS: ADIPIC ACID; STARCH, CORN; CROSPOVIDONE; DEXTROSE, UNSPECIFIED FORM; FD&C BLUE NO. 1; FD&C RED NO. 40; MAGNESIUM STEARATE; MALTODEXTRIN; SUCROSE; TALC

Equate Ultra Strength Antacid Assorted Berry Chewable Tablets

ACTIVE INGREDIENT (in each tablet)

Calcium carbonate 1000 mg

PURPOSE

Antacid

USE(S)

relieves:

- acid indigestion
- heartburn

WARNINGS

.

ASK A DOCTOR OR PHARMACIST BEFORE USE IF YOU ARE

- presently taking a prescription drug. Antacids may interact with certain prescription drugs.

WHEN USING THIS PRODUCT

do not take more than 7 tablets in a 24-hour period, or use the maximum dosage of this product for more than 2 weeks, except under the advice and supervision of a doctor.

IF PREGNANT OR/BREASTFEEDING,

ask a health professional before use.

KEEP OUT OF REACH OF CHILDREN

.

DIRECTIONS

- adults and children 12 years of age and over: chew 2-3 tablets as symptoms occur, or as directed by a doctor.

OTHER INFORMATION

- each tablet contains: elemental calcium 400 mg
- do not use if printed seal under the cap is torn or missing
- store at room temperature. keep the container tightly closed.

INACTIVE INGREDIENTS

adipic acid, corn starch, crospovidone, dextrose, FD&C blue 1 lake, FD&C red 40 lake, flavors, magnesium stearate, maltodextrin, sucrose, talc.

PRINCIPAL DISPLAY PANEL

NDC 49035-778-80
equate
Compare to the active ingredient in Tums Ultra Strength*
ULTRA STRENGTH
Antacid
Tablets
Calcium Carbonate 1000 mg
Assorted Berry Flavors
265 CHEWABLE TABLETS
1000 mg